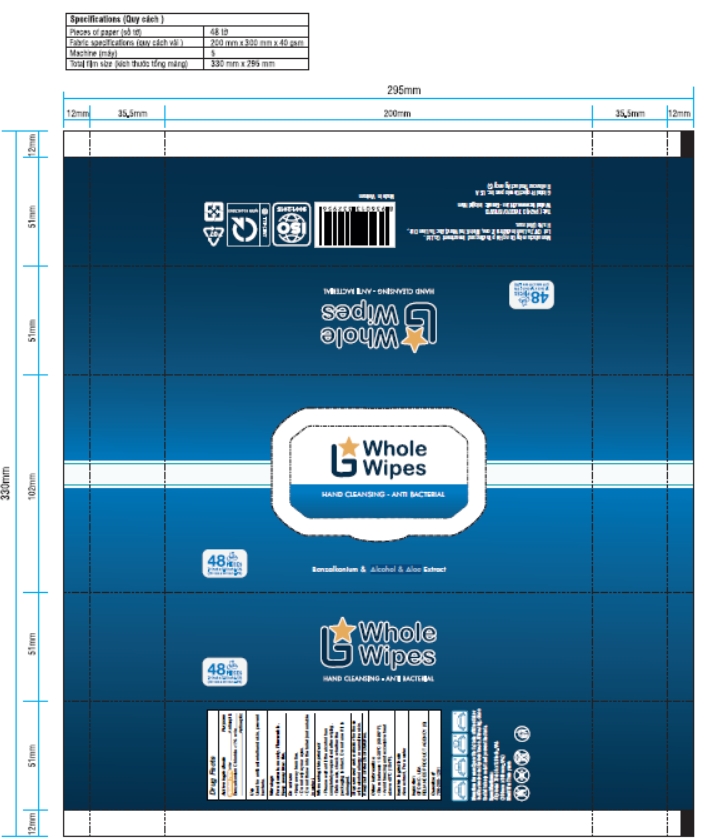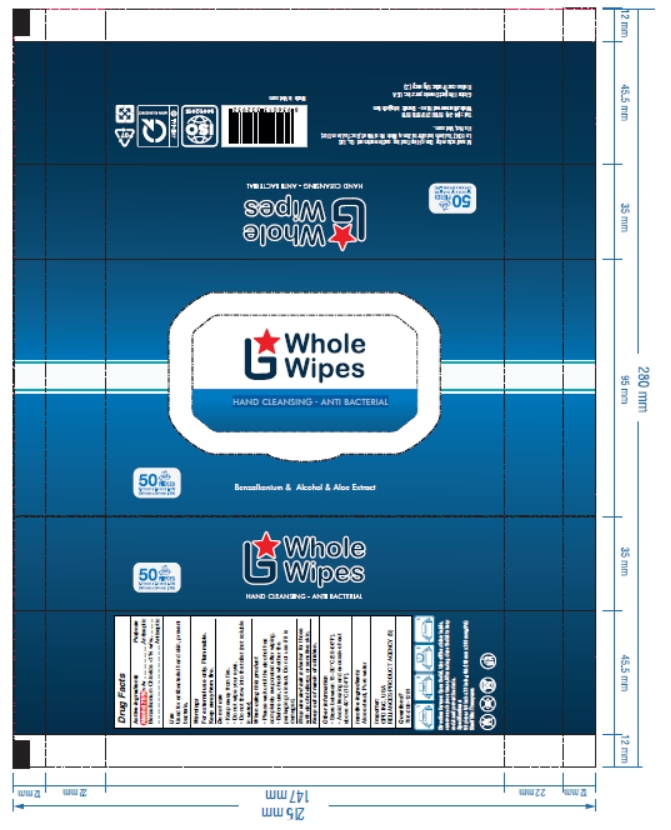 DRUG LABEL: Whole Wipes
NDC: 79366-106 | Form: CLOTH
Manufacturer: Dong Hiep Trading and Investment Co., Ltd
Category: otc | Type: HUMAN OTC DRUG LABEL
Date: 20200901

ACTIVE INGREDIENTS: ALCOHOL 75 mL/100 g; BENZALKONIUM CHLORIDE 1 g/100 g
INACTIVE INGREDIENTS: ALOE; WATER

ACTIVE INGREDIENT

Alcohol 75%

Benzalkonium Chloride <1%

PURPOSE

Antiseptic

INDICATIONS AND USAGE

Used for antibacterial hand skin, prevent bacteria.

WARNINGS

For external use only.

Flammable.

Keep away from fire.

DO NOT USE

• Keep away from fire.
• Do not wipe your eyes.
• Do not throw into the toilet (not soluble in water).

WHEN USING

• Please wait until the alcohol has completely evaporated after wiping.
• Before use, check whether the packaging is intact.

Do not use if it is damaged.

Stop use and ask a doctor for those with alcohol allergy or sensitive skin.

Keep out of reach of children.

STORAGE AND HANDLING

• Store between 15-30°C (59-86°F).
• Avoid freezing and excessive heat above 40°C (104°F).

INACTIVE INGREDIENT

Aloe extract, Pure water